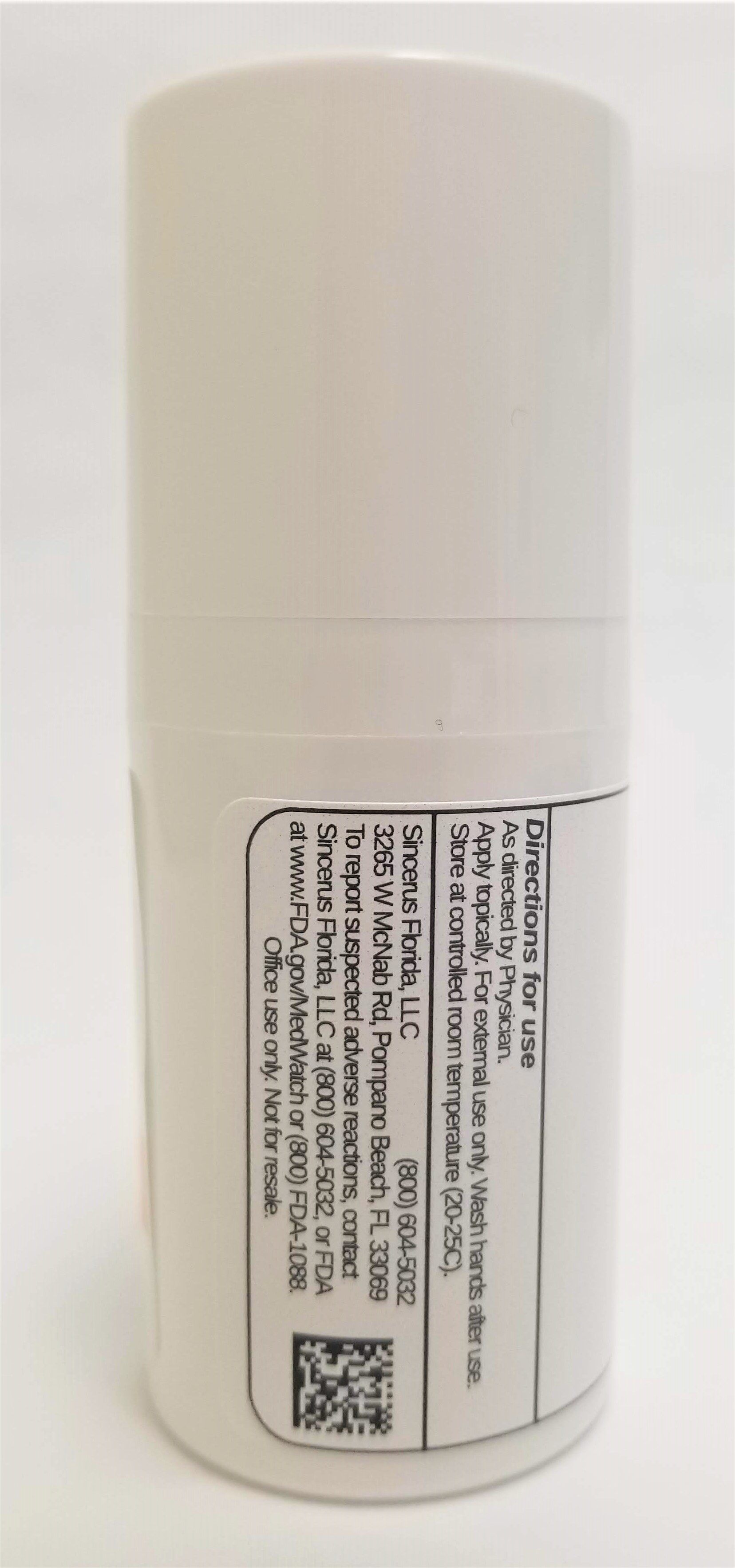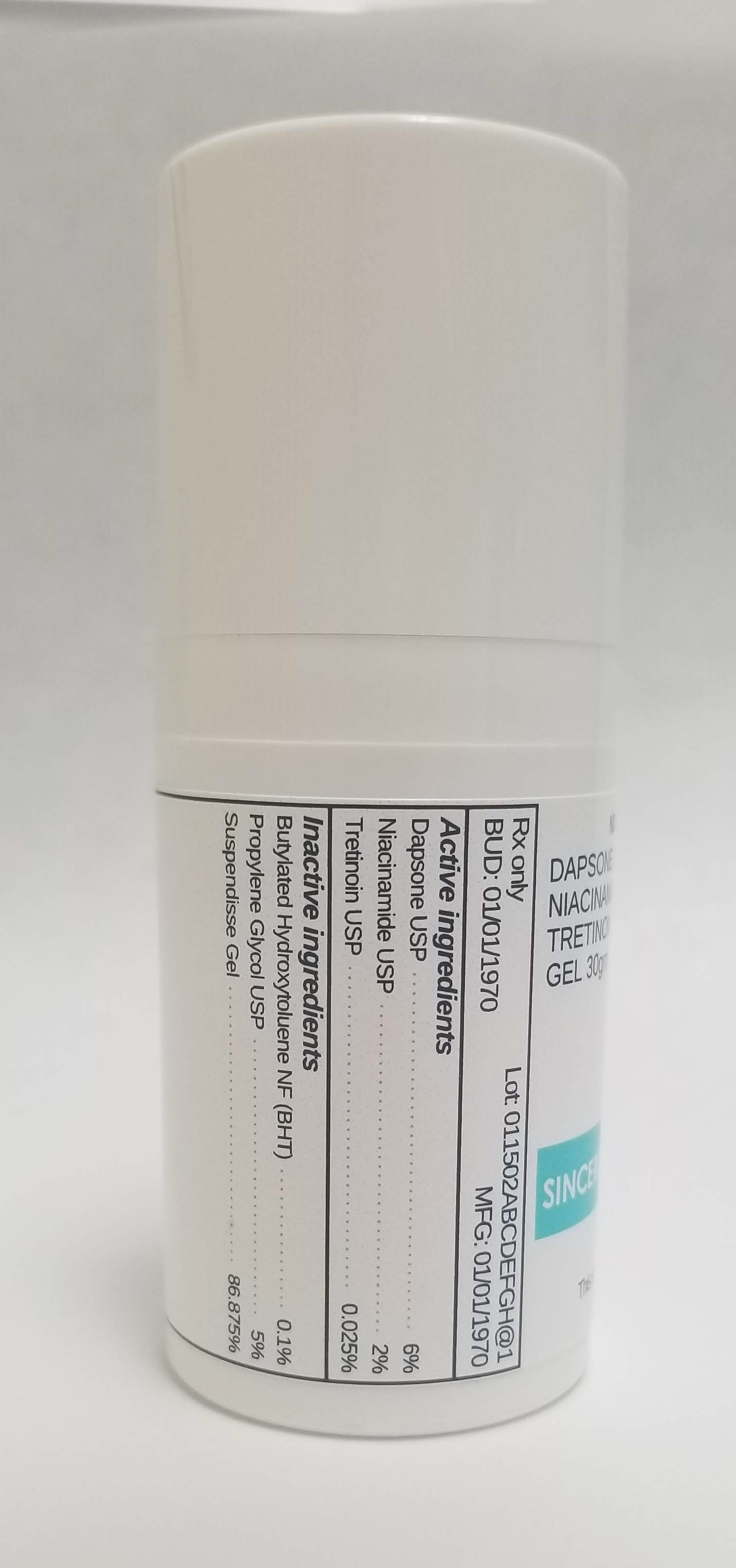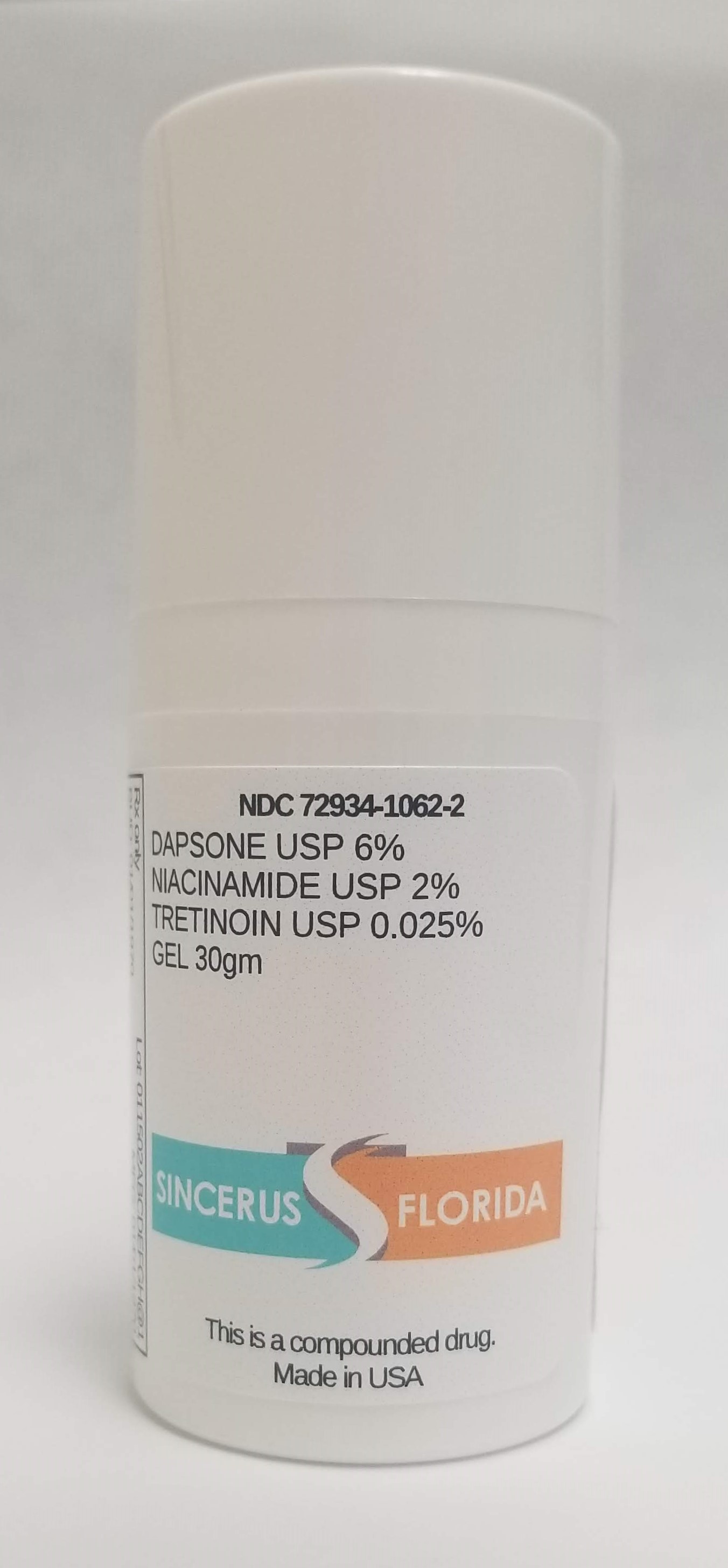 DRUG LABEL: DAPSONE 6% / NIACINAMIDE 2% / TRETINOIN 0.025%
NDC: 72934-1062 | Form: GEL
Manufacturer: Sincerus Florida, LLC
Category: prescription | Type: HUMAN PRESCRIPTION DRUG LABEL
Date: 20190503

ACTIVE INGREDIENTS: NIACINAMIDE 2 g/100 g; DAPSONE 6 g/100 g; TRETINOIN 0.025 g/100 g

DAPSONE 6% / NIACINAMIDE 2% / TRETINOIN 0.025%